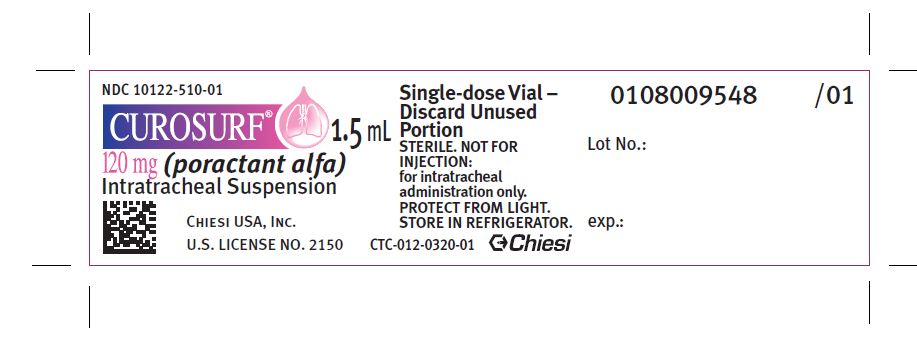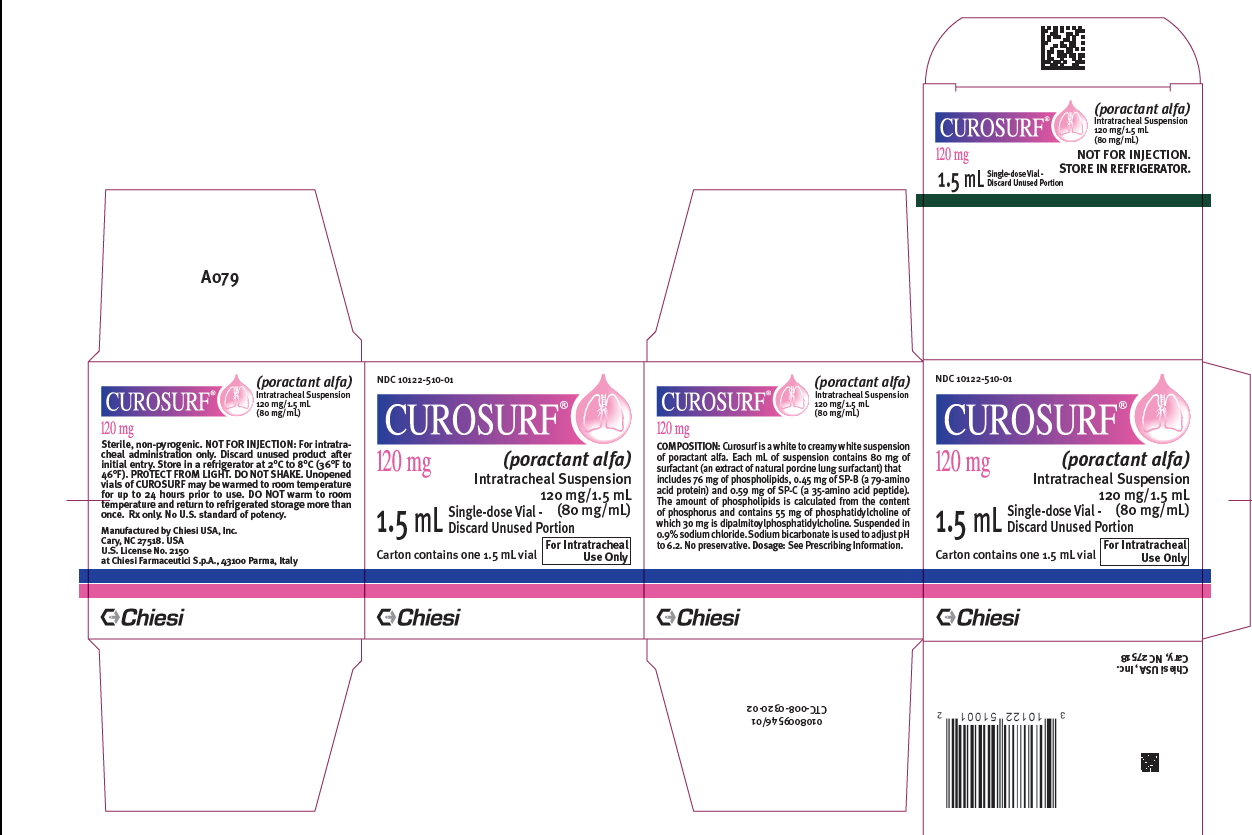 DRUG LABEL: Curosurf
NDC: 10122-510 | Form: SUSPENSION
Manufacturer: Chiesi USA, Inc.
Category: prescription | Type: HUMAN PRESCRIPTION DRUG LABEL
Date: 20251210

ACTIVE INGREDIENTS: PORACTANT ALFA 80 mg/1 mL
INACTIVE INGREDIENTS: SODIUM CHLORIDE; SODIUM BICARBONATE

HIGHLIGHTS OF PRESCRIBING INFORMATION

These highlights do not include all the information needed to use CUROSURF® safely and effectively. See full prescribing information for CUROSURF.
CUROSURF (poractant alfa) intratracheal suspension
Initial U.S. Approval: 1999

1 INDICATIONS AND USAGE

CUROSURF is a surfactant indicated for the rescue treatment, including the reduction of mortality and pneumothoraces, of Respiratory Distress Syndrome (RDS) in premature infants. (1)

2 DOSAGE AND ADMINISTRATION

- Before administering CUROSURF, assure proper placement and patency of endotracheal tube (2.1)
- Administer intratracheally either in (2.1):
  - Two divided aliquots through a 5 French end-hole catheter; or
  - A single bolus through secondary lumen of a dual lumen endotracheal tube without interrupting mechanical ventilation
- Initial recommended dose is 2.5 mL/kg birth weight (2.2)
- Up to two repeat doses of 1.25 mL/kg birth weight may be administered at approximately 12-hour intervals (2.2)
- Maximum total dose (initial plus repeat doses) is 5 mL/kg (2.2)
- See Full Prescribing Information for instructions on preparation and administration of the CUROSURF suspension (2.3, 2.4)

3 DOSAGE FORMS AND STRENGTHS

Intratracheal Suspension:

- 120 mg/1.5 mL (80 mg/mL) single-dose vials (3)
- 240 mg/3 mL (80 mg/mL) single-dose vials (3)

4 CONTRAINDICATIONS

None.

5 WARNINGS AND PRECAUTIONS

- Acute Changes in Lung Compliance: Frequently assess need to modify oxygen and ventilatory support to respiratory changes (5.1)
- Administration-Related Adverse Reactions: Transient adverse effects include bradycardia, hypotension, endotracheal tube blockage, and oxygen desaturation. These events require stopping CUROSURF administration and taking appropriate measures to alleviate the condition (5.2)

6 ADVERSE REACTIONS

- Common adverse reactions associated with the administration of CUROSURF include bradycardia, hypotension, endotracheal tube blockage, and oxygen desaturation. (6)

To report SUSPECTED ADVERSE REACTIONS, contact Chiesi USA, Inc. at 1-888-661-9260 or FDA at 1-800-FDA-1088 or www.fda.gov/medwatch.

FULL PRESCRIBING INFORMATION

1 INDICATIONS AND USAGE

CUROSURF® (poractant alfa) Intratracheal Suspension is indicated for the rescue treatment of Respiratory Distress Syndrome (RDS) in premature infants. CUROSURF reduces mortality and pneumothoraces associated with RDS.

2 DOSAGE AND ADMINISTRATION

2.1 Important Administration Instructions

For intratracheal administration only.

CUROSURF should be administered by, or under the supervision of clinicians experienced in intubation, ventilator management, and general care of premature infants. Before administering CUROSURF, assure proper placement and patency of the endotracheal tube. At the discretion of the clinician, the endotracheal tube may be suctioned before administering CUROSURF. Allow the infant to stabilize before proceeding with dosing.

Administer CUROSURF either:

- Intratracheally by instillation in two divided aliquots through a 5 French end-hole catheter or
- Intratracheally in a single bolus through the secondary lumen of a dual lumen endotracheal tube without interrupting mechanical ventilation.

2.2 Recommended Dosage

The initial recommended dose is 2.5 mL/kg birth weight, administered as one or two aliquots depending upon the instillation procedure [see Dosage and Administration (2.4)].

Up to two repeat doses of 1.25 mL/kg birth weight each may be administered at approximately 12-hour intervals in infants in whom RDS is considered responsible for their persisting or deteriorating respiratory status. The maximum recommended total dosage (sum of the initial and up to two repeat doses) is 5 mL/kg.

2.3 Preparation of the CUROSURF Suspension

1. Remove the vial of CUROSURF suspension from a refrigerator at +2°C to +8°C (36°F to 46°F) and slowly warm the vial to room temperature before use.
2. Visually inspect the CUROSURF suspension for discoloration prior to administration. The color of the CUROSURF suspension should be white to creamy white. Discard the CUROSURF vial if the suspension is discolored.
3. Gently turn the vial upside-down, in order to obtain a uniform suspension. DO NOT SHAKE.
4. Locate the notch (FLIP UP) on the colored plastic cap and lift the notch and pull upwards.
5. Pull the plastic cap with the aluminum portion downwards.
6. Remove the whole ring by pulling off the aluminum wrapper.
7. Remove the rubber cap to extract content.
8. Unopened, unused vials of CUROSURF suspension that have warmed to room temperature can be returned to refrigerated storage within 24 hours for future use. Do not warm to room temperature and return to refrigerated storage more than once. Protect from light.

2.4 Administration

For endotracheal tube instillation using a 5 French end-hole catheter

1. Slowly withdraw the entire contents of the vial of CUROSURF suspension into a 3 or 5 mL plastic syringe through a large-gauge needle (e.g., at least 20 gauge). Enter each single-use vial only once.
2. Attach the 5 French end-hole catheter of appropriate length to position the catheter tip proximal to the distal portion of the endotracheal tube, to the syringe. Fill the catheter with CUROSURF suspension. Discard excess CUROSURF through the catheter so that only the dose to be given remains in the syringe.
  - For the first dose: 1.25 mL/kg (birth weight) per aliquot
  - For each repeated dose: 0.625 mL/kg (birth weight) per aliquot
3. First aliquot of CUROSURF suspension:
  1. Position the infant in a neutral position (head and body in alignment without inclination), with either the right or left side dependent.
  2. Immediately before CUROSURF administration, ventilate the infant with supplemental oxygen sufficient to maintain SaO2 > 92%.
  3. Insert the catheter into the endotracheal tube and instill the first aliquot of CUROSURF suspension.
  4. After the first aliquot is instilled, remove the catheter from the endotracheal tube and manually ventilate with supplemental oxygen until clinically stable.
4. Second aliquot of CUROSURF suspension:
  1. When the infant is stable, reposition the infant such that the other side is dependent.
  2. Administer the remaining aliquot using the same procedures as the first aliquot.
5. After completion of the dosing procedure, do not suction airways for 1 hour after surfactant instillation unless signs of significant airway obstruction occur [see Clinical Studies (14.1)].

For endotracheal tube instillation using the secondary lumen of a dual lumen endotracheal tube

1. Slowly withdraw the entire contents of the vial of CUROSURF suspension into a 3 or 5 mL plastic syringe through a large-gauge needle (e.g., at least 20 gauge). Do not attach 5 French end-hole catheter. Remove the needle and discard excess CUROSURF so that only the dose to be given remains in the syringe.
2. Keep the infant in a neutral position (head and body in alignment without inclination).
3. Administer CUROSURF suspension through the proximal end of the secondary lumen of the endotracheal tube as a single dose, given over 1 minute, and without interrupting mechanical ventilation.
4. After completion of this dosing procedure, ventilator management may require transient increases in FiO2 , ventilator rate, or PIP. Do not suction airways for 1 hour after surfactant instillation unless signs of significant airway obstruction occur.

3 DOSAGE FORMS AND STRENGTHS

Intratracheal suspension: CUROSURF (poractant alfa) is a white to creamy white suspension available in:

- 120 mg/1.5 mL (80 mg/mL) single-dose vials
- 240 mg/3 mL (80 mg/mL) single-dose vials

4 CONTRAINDICATIONS

None.

5 WARNINGS AND PRECAUTIONS

5.1 Acute Changes in Oxygenation and Lung Compliance

The administration of exogenous surfactants, including CUROSURF, can rapidly affect oxygenation and lung compliance. Therefore, infants receiving CUROSURF should receive frequent clinical and laboratory assessments so that oxygen and ventilatory support can be modified to respond to respiratory changes. CUROSURF should only be administered by those trained and experienced in the care, resuscitation, and stabilization of pre-term infants.

5.2 Administration-Related Adverse Reactions

Transient adverse reactions associated with administration of CUROSURF include bradycardia, hypotension, endotracheal tube blockage, and oxygen desaturation. These events require stopping CUROSURF administration and taking appropriate measures to alleviate the condition. After the patient is stable, dosing may proceed with appropriate monitoring.

6 ADVERSE REACTIONS

6.1 Clinical Trials Experience

Because clinical studies are conducted under widely varying conditions, adverse reaction rates observed in the clinical studies of a drug cannot be directly compared to rates in the clinical studies of another drug and may not reflect the rates observed in practice.

Adverse Reactions in Studies in Premature Infants with Respiratory Distress Syndrome

The safety data described below reflect exposure to CUROSURF at a single dose of 2.5 mL/kg (200 mg/kg), in 78 infants of 700-2000 grams birth weight with RDS requiring mechanical ventilation and a FiO2 ≥ 0.60 (Study 1) [see Clinical Studies (14.1)]. A total of 144 infants were studied after RDS developed and before 15 hours of age; 78 infants received CUROSURF 2.5 mL/kg single dose (200 mg/kg), and 66 infants received control treatment (disconnection from the ventilator and manual ventilation for 2 minutes).

Transient adverse reactions seen with the administration of CUROSURF included bradycardia, hypotension, endotracheal tube blockage, and oxygen desaturation. The rates of the most common serious complications associated with prematurity and RDS observed in Study 1 are shown in Table 1.

Table 1: Most Common Serious Complications Associated with Prematurity and RDS in Study 1

 | CUROSURF 2.5 mL/kgn=78 | CONTROL*n=66
Acquired Pneumonia | 17% | 21%
Acquired Septicemia | 14% | 18%
Bronchopulmonary Dysplasia | 18% | 22%
Intracranial Hemorrhage | 51% | 64%
Patent Ductus Arteriosus | 60% | 48%
Pneumothorax | 21% | 36%
Pulmonary Interstitial Emphysema | 21% | 38%

*Control patients were disconnected from the ventilator and manually ventilated for 2 minutes. No surfactant was instilled.

Seventy-six infants (45 treated with CUROSURF) from study 1 were evaluated at 1 year of age and 73 infants (44 treated with CUROSURF) were evaluated at 2 years of age to assess for potential long-term adverse reactions. Data from follow-up evaluations for weight and length, persistent respiratory symptoms, incidence of cerebral palsy, visual impairment, or auditory impairment was similar between treatment groups. In 16 patients (10 treated with CUROSURF and 6 controls) evaluated at 5.5 years of age, the developmental quotient, derived using the Griffiths Mental Developmental Scales, was similar between groups.

6.2 Immunogenicity

Immunological studies have not demonstrated differences in levels of surfactant-anti-surfactant immune complexes and anti-CUROSURF antibodies between patients treated with CUROSURF and patients who received control treatment.

6.3 Postmarketing Experience

Pulmonary hemorrhage, a known complication of premature birth and very low birth-weight, has been reported both in clinical trials with CUROSURF and in postmarketing adverse event reports in infants who had received CUROSURF.

8 USE IN SPECIFIC POPULATIONS

8.4 Pediatric Use

The safety and effectiveness of CUROSURF for the rescue treatment, including the reduction of mortality and pneumothoraces, of Respiratory Distress Syndrome (RDS) have been established in premature infants and the information on this use is discussed throughout the labeling.

The safety and effectiveness of CUROSURF in the treatment of full term infants or older pediatric patients with respiratory failure has not been established.

10 OVERDOSAGE

There have been no reports of overdosage following the administration of CUROSURF.

In the event of accidental overdosage, and if there are clear clinical effects on the infant's respiration, ventilation, or oxygenation, aspirate as much of the suspension as possible and provide the infant with supportive treatment, with particular attention to fluid and electrolyte balance.

11 DESCRIPTION

Poractant alfa is an extract of natural porcine lung (pulmonary) surfactant consisting of 99% polar lipids (mainly phospholipids) and 1% hydrophobic low molecular weight surfactant associated proteins (SP). The molecular weight of SP-B is 8.7 KDa and the molecular weight of SP-C is 3.7 KDa.

CUROSURF (poractant alfa) intratracheal suspension is a sterile, white to creamy white suspension provided in a single-dose vial for intratracheal use. Each milliliter of suspension contains 80 mg of poractant alfa (surfactant extract) that includes 76 mg of phospholipids and 1 mg of SP of which 0.45 mg is SP-B, a 79-amino acid protein and 0.59 mg is SP-C, a 35-amino acid peptide . The amount of phospholipids is calculated from the content of phosphorus and contains 55 mg of phosphatidylcholine of which 30 mg is dipalmitoylphosphatidylcholine. It is suspended in 0.9% sodium chloride solution. The pH is adjusted with sodium bicarbonate to a pH of 6.2 (5.5 to 6.5).

Curosurf contains no preservatives.

12 CLINICAL PHARMACOLOGY

12.1 Mechanism of Action

Endogenous pulmonary surfactant reduces surface tension at the air-liquid interface of the alveoli during ventilation and stabilizes the alveoli against collapse at resting transpulmonary pressures. A deficiency of pulmonary surfactant in preterm infants results in Respiratory Distress Syndrome (RDS) characterized by poor lung expansion, inadequate gas exchange, and a gradual collapse of the lungs (atelectasis).

CUROSURF compensates for the deficiency of surfactant and restores surface activity to the lungs of these infants.

12.2 Pharmacodynamics

In vitro - CUROSURF lowers minimum surface tension to ≤ 4mN/m as measured by the Wilhelmy Balance System.

12.3 Pharmacokinetics

CUROSURF is administered directly to the lung, where biophysical effects occur at the alveolar surface. No human pharmacokinetic studies have been performed to characterize the absorption, biotransformation, or elimination of CUROSURF.

13 NONCLINICAL TOXICOLOGY

13.1 Carcinogenesis, Mutagenesis, Impairment of Fertility

Studies to assess potential carcinogenic effects of CUROSURF have not been conducted.

Poractant alfa was negative for genotoxicity in the following assays: bacterial reverse mutation assay (Ames test), gene mutation assay in Chinese hamster V79 cells, chromosomal aberration assay in Chinese hamster ovary cells, unscheduled DNA synthesis in HELA S3 cells, and in vivo mouse micronucleus assay.

No studies to assess reproductive effects of CUROSURF have been performed.

14 CLINICAL STUDIES

14.1 Rescue Treatment of Respiratory Distress Syndrome

The clinical efficacy of CUROSURF in the treatment of established Respiratory Distress Syndrome (RDS) in premature infants was demonstrated in one single-dose study (Study 1) and one multiple-dose study (Study 2) involving approximately 500 infants. Each study was randomized, multicenter, and controlled.

In study 1, premature infants 700 to 2000 grams birth weight with RDS requiring mechanical ventilation and a FiO2 ≥ 0.60 were enrolled. CUROSURF 2.5 mL/kg single dose (200 mg/kg) or control (disconnection from the ventilator and manual ventilation for 2 minutes) was administered after RDS developed and before 15 hours of age. The results from Study 1 are shown below in Table 2.

Table 2: Study 1 Results in Premature Infants with Respiratory Distress Syndrome

Efficacy Parameter | Single DoseCUROSURFn=78 | Controln=67 | p-Value
Mortality at 28 Days (All Causes) | 31% | 48% | ≤0.05
Bronchopulmonary Dysplasia* | 18% | 22% | N.S.
Pneumothorax | 21% | 36% | ≤0.05
Pulmonary Interstitial Emphysema | 21% | 38% | ≤0.05

*Bronchopulmonary dysplasia (BPD) diagnosed by positive x-ray and supplemental oxygen dependence at 28 days of life.

N.S.: not statistically significant

In Study 2, premature infants 700 to 2000 g birth weight with RDS requiring mechanical ventilation and a FiO2 ≥ 0.60 were enrolled. In this two-arm trial, CUROSURF was administered after RDS developed and before 15 hours of age, as a single-dose or as multiple doses. In the single-dose arm, infants received CUROSURF 2.5 mL/kg (200 mg/kg). In the multiple-dose arm, the initial dose of CUROSURF was 2.5 mL/kg followed by up to two 1.25 mL/kg (100 mg/kg) doses of CUROSURF. The results from Study 2 are shown below in Table 3.

Table 3: Study 2 Results in Premature Infants with Respiratory Distress Syndrome

Efficacy Parameter | Single DoseCUROSURFn=184Rate (%) | Multiple DoseCUROSURFn=173Rate (%) | p-Value
Mortality at 28 Days (All Causes) | 21 | 13 | 0.048
Bronchopulmonary Dysplasia* | 18 | 18 | N.S.
Pneumothorax | 17 | 9 | 0.03
Pulmonary Interstitial Emphysema | 27 | 22 | N.S.

*Bronchopulmonary dysplasia (BPD) diagnosed by positive x-ray and supplemental oxygen dependence at 28 days of life.

N.S.: not statistically significant

There is no controlled experience on the effects of administering initial doses of CUROSURF other than 2.5 mL/kg (200 mg/kg), subsequent doses other than 1.25 mL/kg (100 mg/kg), administration of more than three total doses, dosing more frequently than every 12 hours, or initiating therapy with CUROSURF more than 15 hours after diagnosing RDS. Adequate data are not available on the use of CUROSURF in conjunction with experimental therapies of RDS, e.g., high-frequency ventilation or extracorporeal membrane oxygenation.

16 HOW SUPPLIED/STORAGE AND HANDLING

CUROSURF (poractant alfa) intratracheal suspension is a white to creamy white suspension available in sterile, rubber-stoppered clear glass vials containing (one vial per carton):

- 120 mg/1.5 mL (80 mg/mL) poractant alfa (surfactant extract) of suspension: NDC Number: 10122-510-01
- 240 mg/3 mL (80 mg/mL) poractant alfa (surfactant extract) of suspension. NDC Number: 10122-510-03

Store CUROSURF intratracheal suspension in a refrigerator at +2°C to +8°C (36°F to 46°F). PROTECT FROM LIGHT. Do not shake. Vials are for single-dose only. After opening the vial discard the unused portion [see Dosage and Administration (2.3)].

Manufactured by:

Chiesi USA, Inc.

Cary, NC 27518

U.S.License No. 2150

Manufactured at and licensed from:

Chiesi Farmaceutici, S.p.A.

Parma, Italy 43100

CTC-007-0320-03-SPL-2